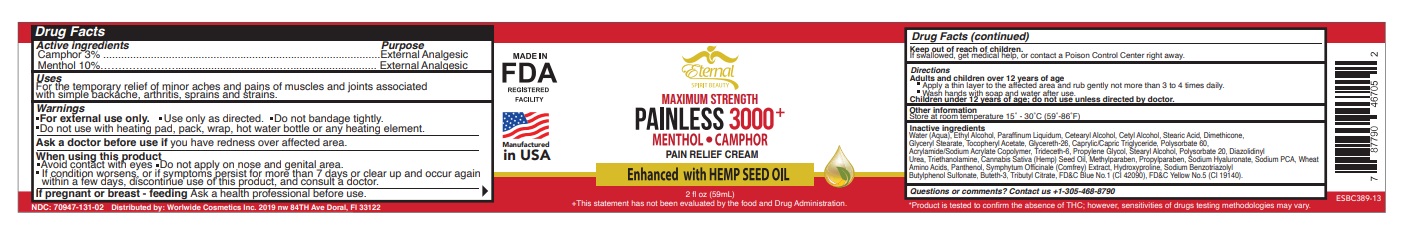 DRUG LABEL: ETERNAL SPIRIT BEAUTY PAIN RELIEF WITH HEMP
NDC: 70947-131 | Form: CREAM
Manufacturer: Worldwide Cosmetics, Inc
Category: otc | Type: HUMAN OTC DRUG LABEL
Date: 20260212

ACTIVE INGREDIENTS: MENTHOL, UNSPECIFIED FORM 10 g/100 g; CAMPHOR (NATURAL) 3 g/100 g
INACTIVE INGREDIENTS: FD&C BLUE NO. 1; SODIUM COCOYL WHEAT AMINO ACIDS; WATER; CETYL ALCOHOL; GLYCERETH-26; METHYLPARABEN; TRIBUTYL CITRATE; BUTETH-3; PANTHENOL; DIAZOLIDINYL UREA; HYALURONATE SODIUM; DIMETHICONE 1000; GLYCERIN; HYDROXYPROLINE; SYMPHYTUM OFFICINALE WHOLE; TRIDECETH-6; SODIUM BENZOTRIAZOLYL BUTYLPHENOL SULFONATE; CETOSTEARYL ALCOHOL; GLYCERYL STEARATE SE; ALCOHOL 95%; ACRYLAMIDE; MINERAL OIL; .ALPHA.-TOCOPHEROL ACETATE, D-; CAPRYLIC/CAPRIC/LAURIC TRIGLYCERIDE; POLYSORBATE 20; PROPYLPARABEN; STEARIC ACID; FD&C YELLOW NO. 5; CANNABIS SATIVA SEED OIL

70947-131-02

ACTIVE INGREDIENT

Menthol 10%
Camphor 3%

PURPOSE

External Analgesic
Pain Relieving

Uses

For the temporary relief of minor aches and pains of muscles and joints associated
with simple backache, arthritis, sprains and strains.

WARNINGS

Use only as directed. For external use only. Do not bandage tightly. Do not use with heating pad,
pack, wrap, hot water bottle or any heating element. Keep away from children. Package not child
resistant. In case of accidental ingestion, contact doctor immediately. If prone to allergic reaction to
the product, consult to a doctor before using.

WHEN USING

Avoid contact with eyes, mucous membranes, rashes, wounds or damaged skin. Do not apply on
nose and genital area. If rash, redness or itchiness results; discontinue use and consult a doctor.

Keep away from children. Package not child
resistant. In case of accidental ingestion, contact doctor immediately.

Directions

Adults and children over 12 years of age;

- apply a thin layer to affected area and rub gently not more than 3 to 4 times a day.
- Wash hands with soap and water after use.

Children under 12 years of age; do not use unless directed by doctor/physician

Other information

Store at room temperature 15° - 30°C (59° - 86°F)

Inactive ingredients

Water (Aqua), Alcohol Denat, Stearic Acid, Paraffinum Liquidum, Cetearyl Alcohol, Polysorbate 60, Cetyl Alcohol, Dimethicone, Glyceryl Stearate, Acrylamide/Sodium Acrylate Copolymer, Trideceth-6, Glycereth-26, Tocopheryl Acetate, Caprylic/Capric Triglyceride, Propylene Glycol, Diazolidinyl Urea, Stearyl Alcohol, Polysorbate 20, Triethanolamine, Cannabis Sativa Seed Oil, Sodium Hyaluronate, Sodium PCA, Wheat Amino Acids, Panthenol, Symphytum Officinale (Comfrey) Extract, Hydroxyproline, Benzotriazolyl Dodecyl p-Cresol, Methylparaben, Propylparaben, FD&C YELLOW No.5 (CI 19140), FD&C Blue No.1 (CI 42090).

Questions or comments?

Contact us +1-305-4688790